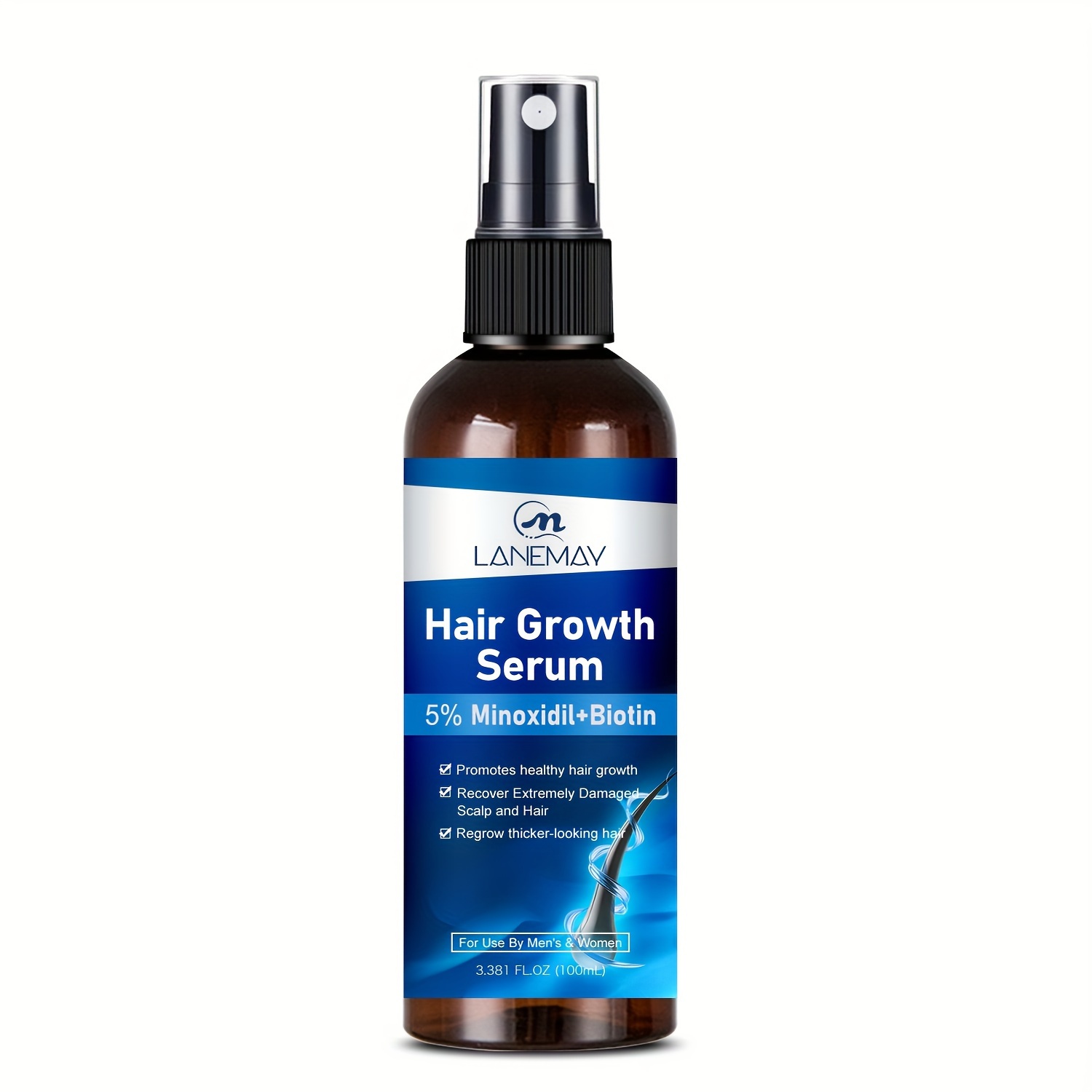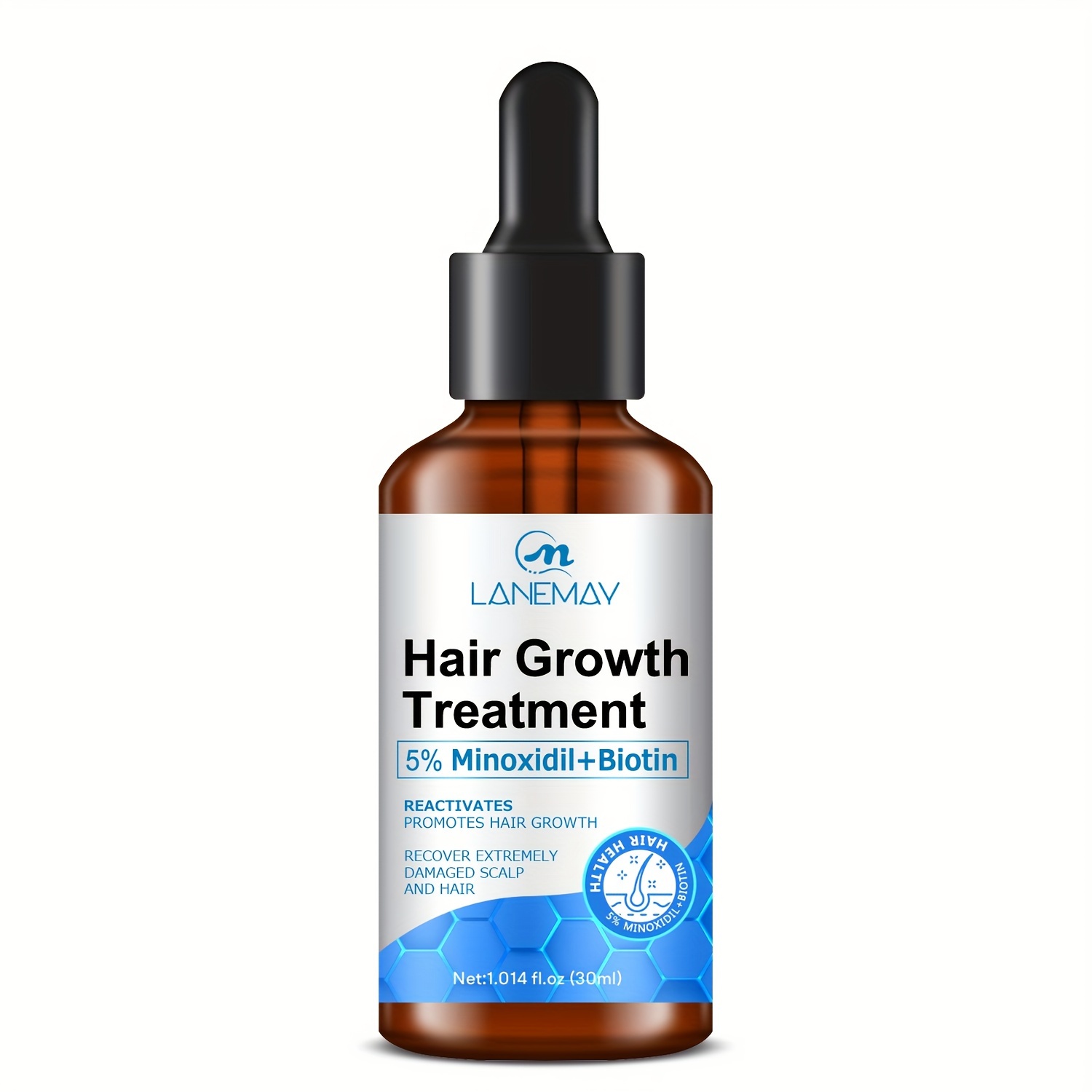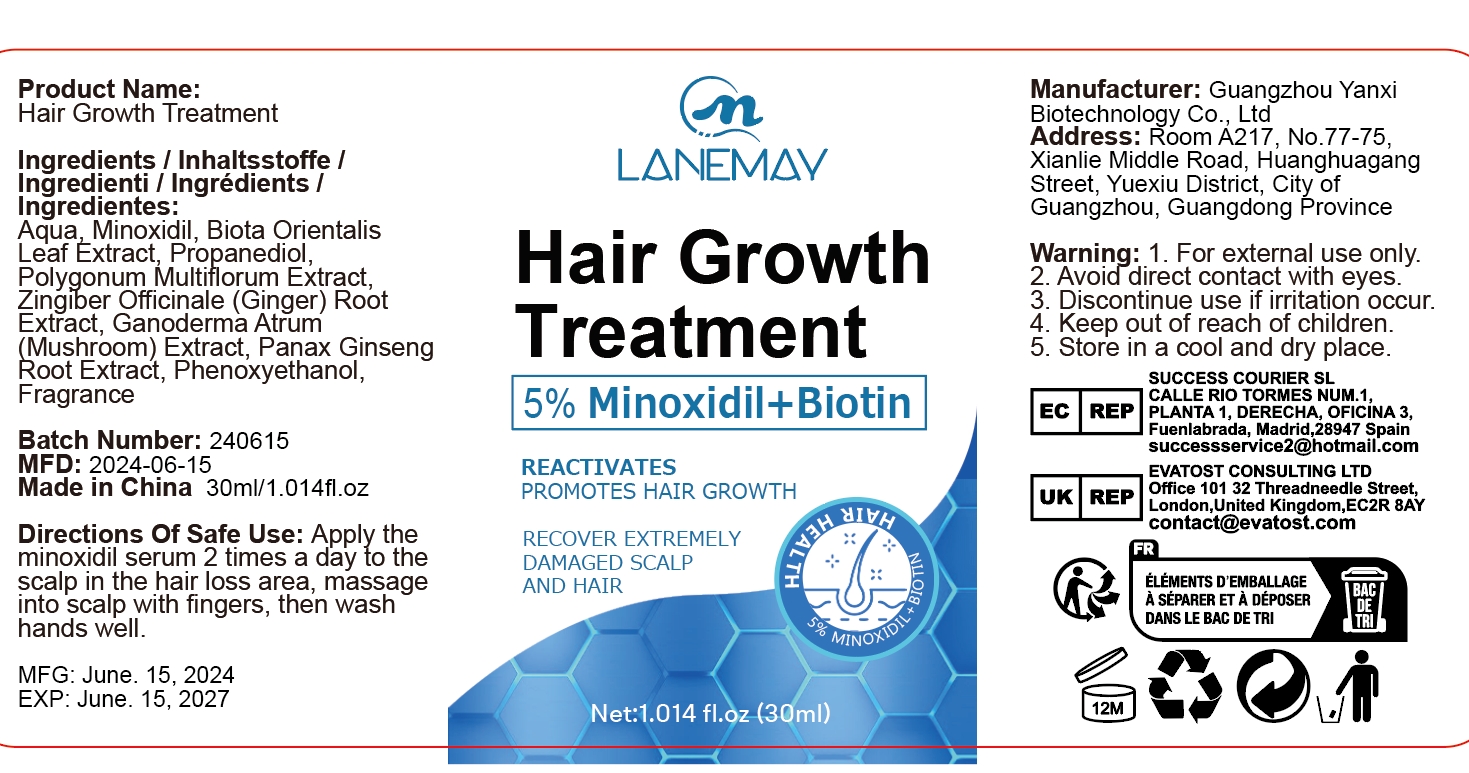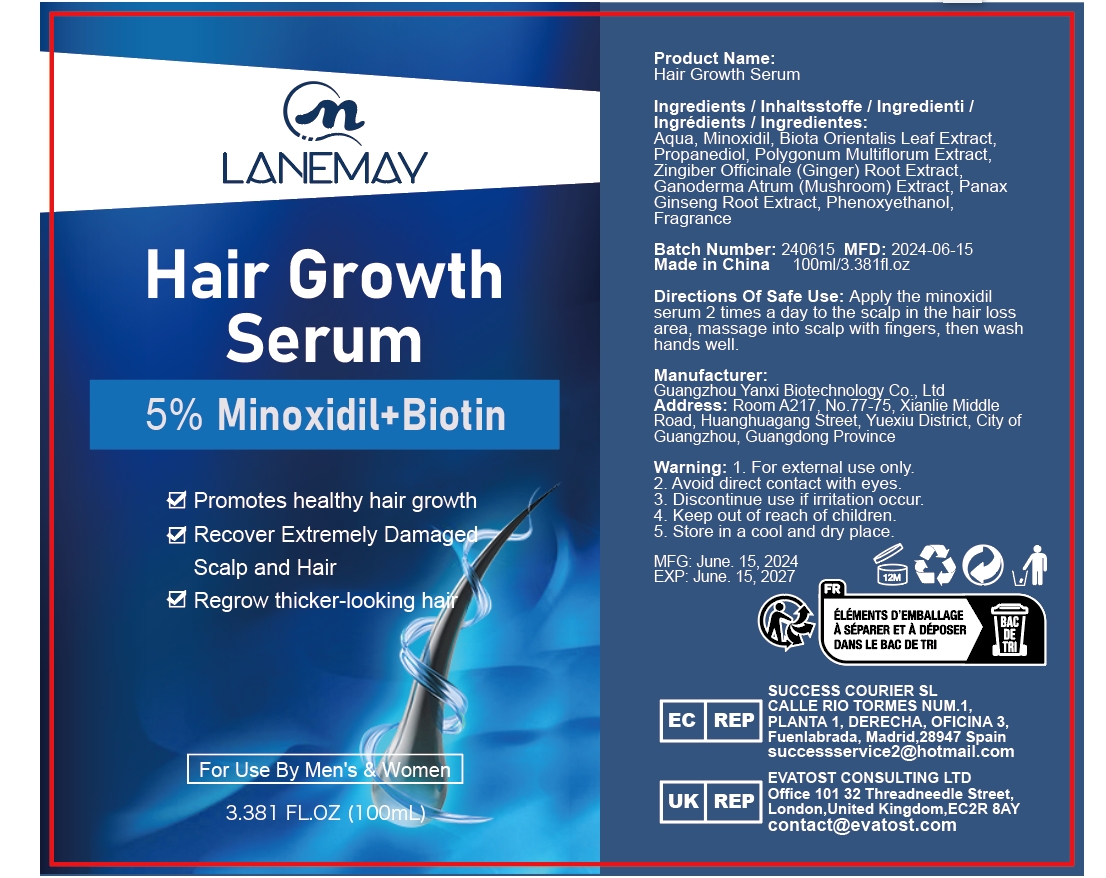 DRUG LABEL: Hair Growth Treatment
NDC: 84025-050 | Form: LIQUID
Manufacturer: Guangzhou Yanxi Biotechnology Co., Ltd
Category: otc | Type: HUMAN OTC DRUG LABEL
Date: 20240626

ACTIVE INGREDIENTS: PROPANEDIOL 2.5 mg/30 mL; PHENOXYETHANOL 2 mg/30 mL
INACTIVE INGREDIENTS: WATER

DOSAGE AND ADMINISTRATION

Apply the minoxidil serum 2 times a day to the scalp in the hair loss area,massage into scalp with fingers,then wash hands well.

WARNINGS

For external use only.

INACTIVE INGREDIENT

aqua

INDICATIONS AND USAGE

For external use only.

Keep out of Children

PURPOSE

hair growth